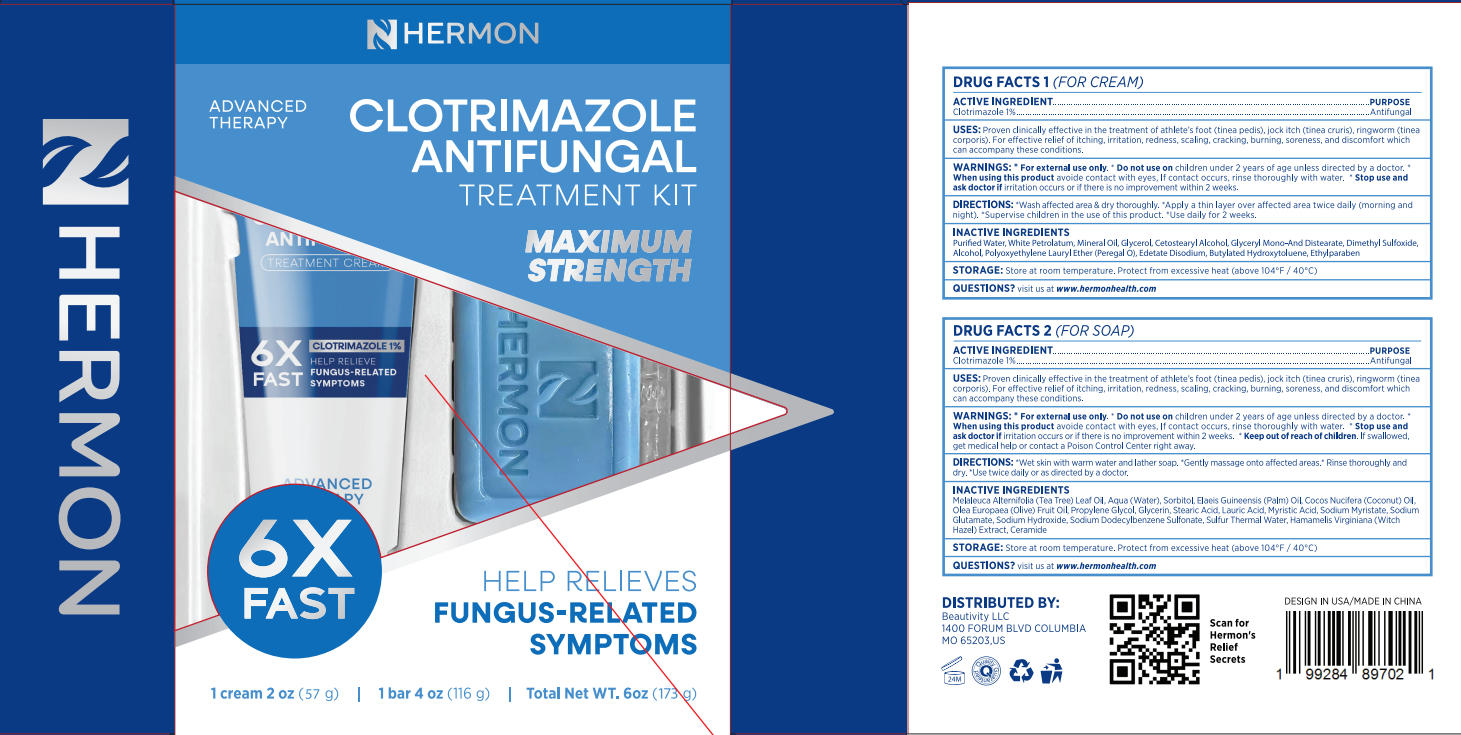 DRUG LABEL: Clotrimazole antifungal treatment kit
NDC: 85398-012 | Form: KIT | Route: TOPICAL
Manufacturer: Beautivity LLC
Category: otc | Type: HUMAN OTC DRUG LABEL
Date: 20250822

ACTIVE INGREDIENTS: CLOTRIMAZOLE 0.57 g/57 g; CLOTRIMAZOLE 1.16 g/116 g
INACTIVE INGREDIENTS: EDETATE DISODIUM; ETHYLPARABEN; WATER; BUTYLATED HYDROXYTOLUENE; GLYCEROL FORMAL; WHITE PETROLATUM; MINERAL OIL; CETOSTEARYL ALCOHOL; DIMETHYL SULFOXIDE; ALCOHOL; MYRISTIC ACID; SODIUM MYRISTATE; SODIUM HYDROXIDE; ELAEIS GUINEENSIS (PALM) OIL; PROPYLENE GLYCOL; LAURIC ACID; HAMAMELIS VIRGINIANA (WITCH HAZEL) LEAF WATER; SODIUM DODECYLBENZENESULFONATE; AQUA; SODIUM GLUTAMATE; MELALEUCA ALTERNIFOLIA (TEA TREE) LEAF OIL; STEARIC ACID; SORBITOL; OLEA EUROPAEA (OLIVE) FRUIT OIL; GLYCERIN; COCOS NUCIFERA (COCONUT) OIL; CERAMIDE 1

Initial Drug Listing - Clotrimazole antifungal treatment kit

ACTIVE INGREDIENT

Clotrimazole 1%

PURPOSE

Antifungal

DOSAGE AND ADMINISTRATION

Proven clinically effective in the treatment of athlete's foot (tinea pedis), jock itch (tinea cruris), ringworm (tineacorporis). For effective relief of itching, irritation, redness, scaling, cracking, burning, soreness, and discomfort which can accompany these conditions.

WARNINGS

For external use only.

Do not use on children under 2 years of age unless directed by a doctor.

WHEN USING

avoide contact with eyes, lf contact occurs, rinse thoroughly with water.

ASK DOCTOR

irritation occurs or if there is no improvement within 2 weeks.

KEEP OUT OF REACH OF CHILDREN

lf swallowed, get medical help or contact a Poison Control Center right away.

INDICATIONS AND USAGE

For cream

- Wash affected area & dry thoroughly.
- Apply a thin layer over affected area twice dally (morning andnight).
- Supervise children in the use of this product.
- Use daily for 2 weeks.

For soap

- Wet skin with warm water and lather soap.
- Gently massage onto affected areas.
- Rinse thoroughly and dry.
- Use twice daily or as directed by a doctor.

INACTIVE INGREDIENT

For cream:

Purifed Water, White Petrolatum, Mineral Oil, Glycerol, Cetostearyl Alcohol, Glyceryl Mono-And Distearate, Dimethyl sulfoxide, Alcohol, Polyoxyethylene Lauryl Ether (Peregal 0), Edetate Disodium, Butylated Hydroxytoluene, Ethylparaben

For soap:

Melaleuca Alternifalla (Tea Tree) Leaf Oil, Aqua (Water), Sorbitol, Elaeis Guineensis (Palm) Olil, Cocos Nucifera (Coconut) Olil,Olea Europaea (0live) Fruit Oi, Propylene Glycol, Glycerin, stearic Acid, Lauric Acid, Myristic Acid, Sodium Myristate, Sodium Glutamate, Sodium Hydroxide, Sodium Dodecylbenzene Sulfonate, Sulfur Thermal Water, Hamamelis Virginiana (WitchHazel)Extract, Ceramide

STORAGE AND HANDLING

Store at room temperature. Protect from excessive heat (above 104°F/ 40°C)

QUESTIONS

visit us at www.hermonhealth.com